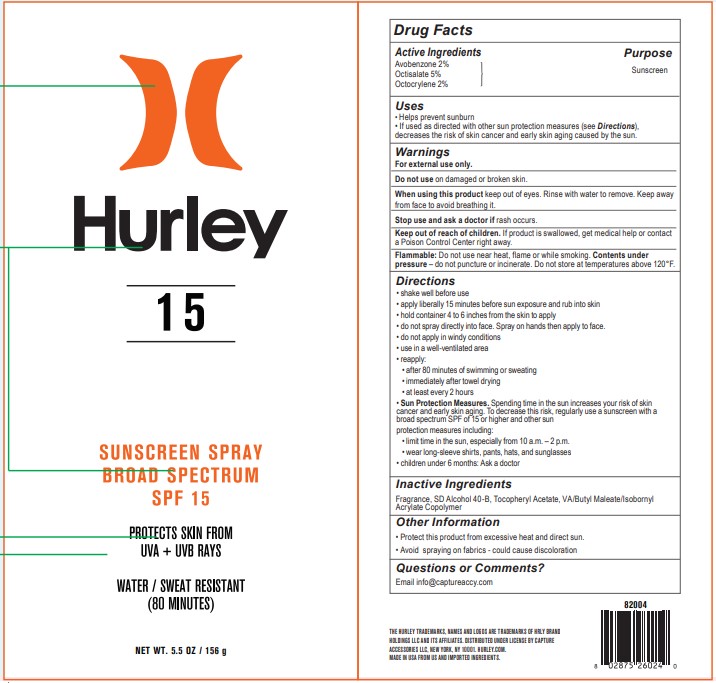 DRUG LABEL: Hurley
NDC: 13630-0251 | Form: SPRAY
Manufacturer: Prime Packaging, Inc.
Category: otc | Type: HUMAN OTC DRUG LABEL
Date: 20220928

ACTIVE INGREDIENTS: AVOBENZONE 16.4 mg/1 mL; OCTISALATE 41.1 mg/1 mL; OCTOCRYLENE 16.4 mg/1 mL
INACTIVE INGREDIENTS: .ALPHA.-TOCOPHEROL ACETATE; ISOBORNYL ACRYLATE; ALCOHOL; VINYL ACETATE; DIBUTYL MALEATE

HURLEY 15 REEF FRIENDLY SUNSCREEN SPRAY BROAD SPECTRUM SPF 15

Active Ingredients

Avobenzone 2%

Octisalate 5%

Octocrylene 2%

Purpose

Sunscreen

Uses

- Helps prevent sunburn.
- If used as directed with other sun protection measures (see Directions), decreases the risk of skin cancer and early skin aging caused by the sun.

Warnings

For external use only.

Do not use on damaged or broken skin.

When using this product keep out of eyes. Rinse with water to remove. Keep away from face to avoid breathing it.

Stop use and ask a doctor if rash occurs.

Keep out of reach of children. If product is swallowed, get medical help or contact a Poison Control Center right away.

OTHER SAFETY INFORMATION

Flammable: Do not use near heat, flame or while smoking. Contents under pressure - do not puncture or incinerate. Do not store at temperatures above 120°F.

Directions

• shake well before use • apply liberally 15 minutes before sun exposure and rub into skin • hold container 4 to 6 inches from the skin to apply • do not spray directly into face. Spray on hands then apply to face • do not apply in windy conditions • use in a well-ventilated area • reapply: • after 80 minutes of swimming or sweating • immediately after towel drying • at least every 2 hours • Sun Protection Measures. Spending time in the sun increases your risk of skin cancer and early skin aging. To decrease this risk, regularly use a sunscreen with a broad spectrum SPF of 15 or higher and other sun protection measures including: • limit time in the sun, especially from 10 a.m. – 2 p.m. • wear long-sleeve shirts, pants, hats, and sunglasses • children under 6 months: Ask a doctor

Inactive ingredients

Fragrance, SD Alcohol 40-B, Tocopheryl Acetate, VA/Butyl Maleate/Isobornyl Acrylate Copolymer.

Other information

• Protect this product from excessive heat and direct sun.

• Avoid spraying on fabrics - could cause discoloration.

Questions or comments?

Email Info@captureaccy.com